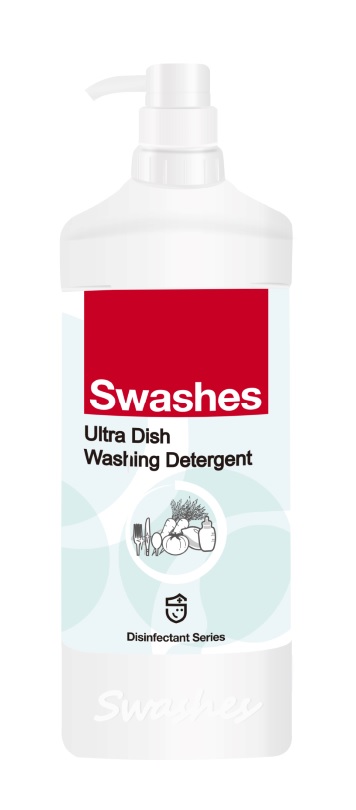 DRUG LABEL: Ultra Dish Washing Detergent
NDC: 74974-008 | Form: LIQUID
Manufacturer: Swashes (Shenzhen) Co., Ltd.
Category: otc | Type: HUMAN OTC DRUG LABEL
Date: 20200409

ACTIVE INGREDIENTS: CHLOROXYLENOL 1 g/1 L
INACTIVE INGREDIENTS: SODIUM HYDROXIDE; SODIUM LAURETH-5 SULFATE; EDETATE SODIUM; SODIUM CHLORIDE; METHYLCHLOROISOTHIAZOLINONE; WATER; DODECYLBENZENESULFONIC ACID; COCO DIETHANOLAMIDE; METHYLISOTHIAZOLINONE

Ultra Dish Washing Detergent 74974-008

Ultra Dish Washing Detergent

Active Ingredient(s)

CHLOROXYLENOL 1g/L

Purpose: Antiseptic

Purpose

Antiseptic, Ultra Dish Washing Detergent

Use

Ultra Dish Washing Detergent to help reduce bacteria that potentially can cause disease. For use when soap and water are not available.

Warnings

For external use only. Flammable. Keep away from heat or flame

Do not use

- in children less than 2 months of age
- on open skin wounds

When using this product keep out of eyes, ears, and mouth. In case of contact with eyes, rinse eyes thoroughly with water.
Stop use and ask a doctor if irritation or rash occurs. These may be signs of a serious condition.
Keep out of reach of children. If swallowed, get medical help or contact a Poison Control Center right away.

Stop use and ask a doctor if irritation or rash occurs. These may be signs of a serious condition.

Keep out of reach of children. If swallowed, get medical help or contact a Poison Control Center right away.

Directions

- Place enough product on hands to cover all surfaces. Rub hands together until dry.
- Supervise children under 6 years of age when using this product to avoid swallowing.

Other information

- Store between 15-30C (59-86F)
- Avoid freezing and excessive heat above 40C (104F)

Inactive ingredients

CHLOROXYLENOL
C18H30O3S
Sodium Hydroxide
Sodium Alcohol Ether Sulphate
Coconut Diethanol Amide
Ethylene diamine tetraacetic acid tetrasodium
Sodium chloride
Kathon.cmit/mit
Purity Water

Package Label - Principal Display Panel

1 L NDC: 74974-008-01